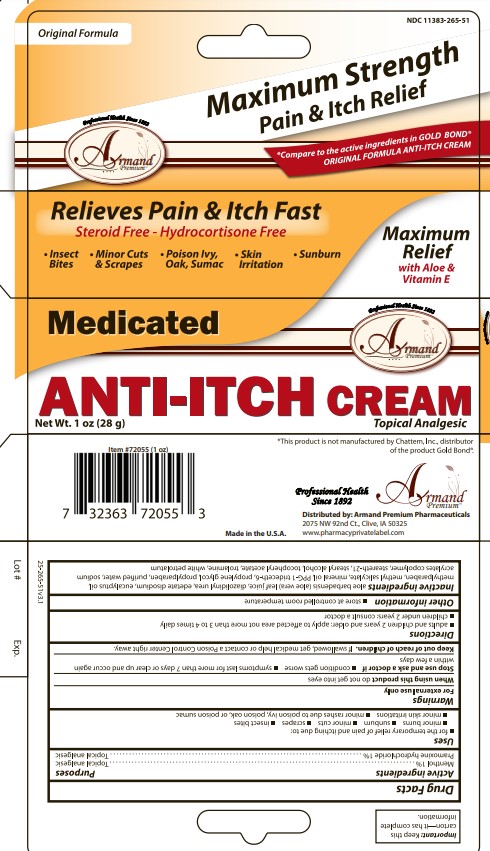 DRUG LABEL: Freds Medicated anti itch
NDC: 11383-265 | Form: CREAM
Manufacturer: Weeks and Leo, Inc.
Category: otc | Type: HUMAN OTC DRUG LABEL
Date: 20241208

ACTIVE INGREDIENTS: PRAMOXINE HYDROCHLORIDE 1 g/100 g; MENTHOL 1 g/100 g
INACTIVE INGREDIENTS: STEARETH-21; .ALPHA.-TOCOPHEROL ACETATE, DL-; SODIUM ACRYLATE; MINERAL OIL; EDETATE DISODIUM; TROLAMINE; PROPYLENE GLYCOL; METHYL SALICYLATE; ALOE VERA LEAF; WATER; PETROLATUM; STEARYL ALCOHOL; PPG-1 TRIDECETH-6; EUCALYPTUS OIL

Armand Medicated Anti itch Cream

Active Ingredient

Menthol 1%

Pramoxine hydrochloride 1%

Uses

for the temporary relief of pain and itching due to: minor burns, sunburn, minor cuts, scrapes, insect bites, minor skin irritations ,minor rashes due to poison ivy, poison oak, or poison sumac

Purpose

Topical anagesic

Warnings

External use only

When using product do not get into eyes

Stop use and ask a doctor if ▪ conditions get worse ▪ symptoms get worse ▪ symptoms last for more than 7 days or clear up and occur again within a few days

Keep out of reach of children. If swallowed, get medical help or contact a Poison Control Center right away.

When using this product

do not get into eyes

Keep out of reach of children

If swallowed, get medical help or contact a Poison Control Center right away.

Other Information

store at controlled room temperature

Directions

adults and children 2 years and older: apply to affected area not more than 3 to 4 times daily

children under 2 years: consult a doctor

DOSAGE AND ADMINISTRATION

Adults and Children 2 years and older: Apply to affected are not more than 3 to 4 times daily.

Inactive Ingredients

aloe barbadensis (aloe vera) leaf juice, diazolidinyl urea, edetate disodium, eucalyptus oil, methylparaben, methyl salicylate, mineral oil, PPG-1 trideceth-6, propylene glycol, propylparaben, purified water, sodium acrylates copolymer, steareth-21, stearyl alcohol, tocopheryl acetate, trolamine, white petrolatum